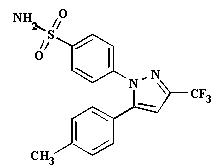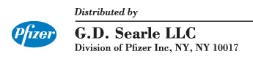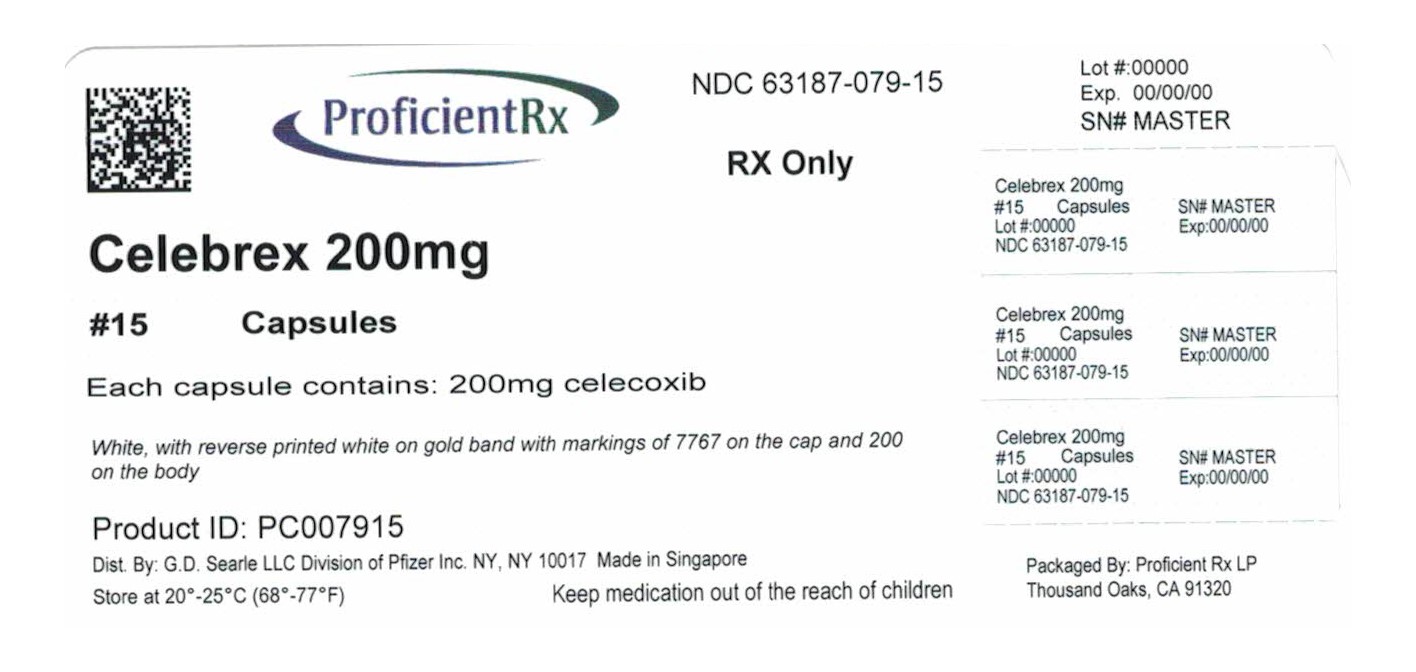 DRUG LABEL: CELEBREX
NDC: 63187-079 | Form: CAPSULE
Manufacturer: Proficient Rx LP
Category: prescription | Type: HUMAN PRESCRIPTION DRUG LABEL
Date: 20210101

ACTIVE INGREDIENTS: CELECOXIB 200 mg/1 1
INACTIVE INGREDIENTS: CROSCARMELLOSE SODIUM; GELATIN, UNSPECIFIED; LACTOSE MONOHYDRATE; MAGNESIUM STEARATE; POVIDONE, UNSPECIFIED; SODIUM LAURYL SULFATE

HIGHLIGHTS OF PRESCRIBING INFORMATION

These highlights do not include all the information needed to use CELEBREX safely and effectively. See full prescribing information for CELEBREX.
CELEBREX ® (celecoxib) capsules
Initial U.S. Approval: 1998

WARNING: CARDIOVASCULAR AND GASTROINTESTINAL RISKS

See full prescribing information for complete boxed warning

Cardiovascular Risk

- CELEBREX may cause an increased risk of serious cardiovascular thrombotic events, myocardial infarction, and stroke, which can be fatal. All NSAIDs may have a similar risk. This risk may increase with duration of use. Patients with cardiovascular disease or risk factors for cardiovascular disease may be at greater risk. (5.1,14.6)
- CELEBREX is contraindicated for the treatment of peri-operative pain in the setting of coronary artery bypass graft (CABG) surgery. (4, 5.1)

Gastrointestinal Risk

- NSAIDs, including CELEBREX, cause an increased risk of serious gastrointestinal adverse events including bleeding, ulceration, and perforation of the stomach or intestines, which can be fatal. These events can occur at any time during use and without warning symptoms. Elderly patients are at greater risk for serious gastrointestinal (GI) events. (5.4)

1.INDICATIONS AND USAGE

CELEBREX is a nonsteroidal anti-inflammatory drug indicated for:
7. Osteoarthritis (OA) (1.1)
8. Rheumatoid Arthritis (RA) (1.2)
9. Juvenile Rheumatoid Arthritis (JRA) in patients 2 years and older (1.3)
10. Ankylosing Spondylitis (AS) (1.4)
11. Acute Pain (AP) (1.5)
12. Primary Dysmenorrhea (PD) (1.6)

2.DOSAGE AND ADMINISTRATION

Use lowest effective dose for the shortest duration consistent with treatment goals for the individual patient. (1, 5.1, 5.4)

- OA: 200 mg once daily or 100 mg twice daily (2.1, 14.1)
- RA: 100 to 200 mg twice daily (2.2, 14.2)
- JRA: 50 mg twice daily in patients 10–25 kg. 100 mg twice daily in patients more than 25 kg (2.3, 14.3)
- AS: 200 mg once daily single dose or 100 mg twice daily. If no effect is observed after 6 weeks, a trial of 400 mg (single or divided doses) may be of benefit (2.4, 14.4)
- AP and PD: 400 mg initially, followed by 200 mg dose if needed on first day. On subsequent days, 200 mg twice daily as needed (2.5, 14.5)

Reduce daily dose by 50% in patients with moderate hepatic impairment (Child-Pugh Class B).

Consider a dose reduction by 50% (or alternative management for JRA) in patients who are known or suspected to be CYP2C9 poor metabolizers, (2.6, 8.4, 8.8, 12.3).

3.DOSAGE FORMS AND STRENGTHS

Capsules: 50 mg, 100 mg, 200 mg and 400 mg (3)

4.CONTRAINDICATIONS

- Known hypersensitivity to celecoxib or sulfonamides (4)
- History of asthma, urticaria, or other allergic-type reactions after taking aspirin or other NSAIDs (4, 5.7, 5.8, 5.13)
- Use during the perioperative period in the setting of coronary artery bypass graft (CABG) surgery (4, 5.1)
- Active gastrointestinal bleeding (4, 5.4)

5.WARNINGS AND PRECAUTIONS

- Serious and potentially fatal cardiovascular (CV) thrombotic events, myocardial infarction, and stroke. Patients with known CV disease/risk factors may be at greater risk (5.1, 14.6, 17.2).
- Serious gastrointestinal (GI) adverse events, which can be fatal. The risk is greater in patients with a prior history of ulcer disease or GI bleeding, and in patients at high risk for GI events, especially the elderly. CELEBREX should be used with caution in these patients (5.4, 8.5, 14.6, 17.3).
- Elevated liver enzymes and, rarely, severe hepatic reactions. Discontinue use of CELEBREX immediately if abnormal liver enzymes persist or worsen (5.5, 17.4).
- New onset or worsening of hypertension. Blood pressure should be monitored closely during treatment with CELEBREX (5.2, 7.4, 17.2).
- Fluid retention and edema. CELEBREX should be used with caution in patients with fluid retention or heart failure (5.3, 17.6).
- Renal papillary necrosis and other renal injury with long term use. Use CELEBREX with caution in the elderly, those with impaired renal function, heart failure, liver dysfunction, and those taking diuretics, ACE-inhibitors, or angiotensin II antagonists (5.6, 7.4, 8.7, 17.6).
- Anaphylactoid reactions. Do not use CELEBREX in patients with the aspirin triad (5.7, 10, 17.7).
- Serious skin adverse events such as exfoliative dermatitis, Stevens-Johnson syndrome (SJS), and toxic epidermal necrolysis (TEN), which can be fatal and can occur without warning even without known prior sulfa allergy. Discontinue CELEBREX at first appearance of rash or skin reactions (5.8, 17.5).

6.ADVERSE REACTIONS

Most common adverse reactions in arthritis trials (>2% and >placebo): abdominal pain, diarrhea, dyspepsia, flatulence, peripheral edema, accidental injury, dizziness, pharyngitis, rhinitis, sinusitis, upper respiratory tract infection, rash (6.1).

To report SUSPECTED ADVERSE REACTIONS, contact Pfizer at 1-800-438-1985 or FDA at 1-800-FDA-1088 or www.fda.gov/medwatch

7.DRUG INTERACTIONS

- Concomitant use of CELEBREX and warfarin may result in increased risk of bleeding complications. (7.1)
- Concomitant use of CELEBREX increases lithium plasma levels. (7.2)
- Concomitant use of CELEBREX may reduce the antihypertensive effect of ACE Inhibitors and angiotensin II antagonists. Concomitant use of CELEBREX with ACE-Inhibitors in elderly or volume depleted or renally compromised patients may result in deterioration of renal function, including acute renal failure. (7.4)
- Use caution with drugs known to inhibit P450 2C9 or metabolized by 2D6 due to the potential for increased plasma levels (2.6, 8.4, 8.8, 12.3)

8.USE IN SPECIFIC POPULATIONS

- Pregnancy Category C prior to 30 weeks gestation; Category D starting at 30 weeks gestation (5.9, 8.1, 17.8)

FULL PRESCRIBING INFORMATION

WARNING: CARDIOVASCULAR AND GASTROINTESTINAL RISKS

Cardiovascular Risk

- CELEBREX may cause an increased risk of serious cardiovascular thrombotic events, myocardial infarction, and stroke, which can be fatal. All nonsteroidal anti-inflammatory drugs (NSAIDs) may have a similar risk. This risk may increase with duration of use. Patients with cardiovascular disease or risk factors for cardiovascular disease may be at greater risk. (5.1,14.6)
- CELEBREX is contraindicated for the treatment of peri-operative pain in the setting of coronary artery bypass graft (CABG) surgery. (4, 5.1)

Gastrointestinal Risk

- NSAIDs, including CELEBREX, cause an increased risk of serious gastrointestinal adverse events including bleeding, ulceration, and perforation of the stomach or intestines, which can be fatal. These events can occur at any time during use and without warning symptoms. Elderly patients are at greater risk for serious gastrointestinal events. (5.4)

1.INDICATIONS AND USAGE

Carefully consider the potential benefits and risks of CELEBREX and other treatment options before deciding to use CELEBREX. Use the lowest effective dose for the shortest duration consistent with individual patient treatment goals [see Warnings and Precautions (5)]

1.1Osteoarthritis (OA)

CELEBREX is indicated for relief of the signs and symptoms of OA [see Clinical Studies (14.1)]

1.2Rheumatoid Arthritis (RA)

CELEBREX is indicated for relief of the signs and symptoms of RA [see Clinical Studies (14.2)]

1.3 Juvenile Rheumatoid Arthritis (JRA)

CELEBREX is indicated for relief of the signs and symptoms of JRA in patients 2 years and older [see Clinical Studies (14.3)]

1.4Ankylosing Spondylitis (AS)

CELEBREX is indicated for the relief of signs and symptoms of AS [see Clinical Studies (14.4)]

1.5Acute Pain (AP)

CELEBREX is indicated for the management of AP in adults [see Clinical Studies (14.5)]

1.6Primary Dysmenorrhea (PD)

CELEBREX is indicated for the treatment of PD [see Clinical Studies (14.5)]

2.DOSAGE AND ADMINISTRATION

Use lowest effective dose for the shortest duration consistent with treatment goals for the individual patient.

These doses can be given without regard to timing of meals.

2.1Osteoarthritis

For relief of the signs and symptoms of OA the recommended oral dose is 200 mg per day administered as a single dose or as 100 mg twice daily.

2.2Rheumatoid Arthritis

For relief of the signs and symptoms of RA the recommended oral dose is 100 to 200 mg twice daily.

2.3Juvenile Rheumatoid Arthritis

For the relief of the signs and symptoms of JRA the recommended oral dose for pediatric patients (age 2 years and older) is based on weight. For patients ≥10 kg to ≤25 kg the recommended dose is 50 mg twice daily. For patients >25 kg the recommended dose is 100 mg twice daily.

For patients who have difficulty swallowing capsules, the contents of a CELEBREX capsule can be added to applesauce. The entire capsule contents are carefully emptied onto a level teaspoon of cool or room temperature applesauce and ingested immediately with water. The sprinkled capsule contents on applesauce are stable for up to 6 hours under refrigerated conditions (2–8° C/ 35–45° F).

2.4Ankylosing Spondylitis

For the management of the signs and symptoms of AS, the recommended dose of CELEBREX is 200 mg daily in single (once per day) or divided (twice per day) doses. If no effect is observed after 6 weeks, a trial of 400 mg daily may be worthwhile. If no effect is observed after 6 weeks on 400 mg daily, a response is not likely and consideration should be given to alternate treatment options.

2.5Management of Acute Pain and Treatment of Primary Dysmenorrhea

The recommended dose of CELEBREX is 400 mg initially, followed by an additional 200 mg dose if needed on the first day. On subsequent days, the recommended dose is 200 mg twice daily as needed.

2.6Special Populations

Hepatic insufficiency: The daily recommended dose of CELEBREX capsules in patients with moderate hepatic impairment (Child-Pugh Class B) should be reduced by 50%. The use of CELEBREX in patients with severe hepatic impairment is not recommended [see Warnings and Precautions (5.5), Use in Specific Populations (8.6) and Clinical Pharmacology (12.3)].

Poor Metabolizers of CYP2C9 Substrates: Patients who are known or suspected to be poor CYP2C9 metabolizers based on genotype or previous history/experience with other CYP2C9 substrates (such as warfarin, phenytoin) should be administered celecoxib with caution. Consider starting treatment at half the lowest recommended dose in poor metabolizers (i.e. CYP2C9*3/*3). Consider using alternative management in JRA patients who are poor metabolizers. [see Use in Specific populations (8.8), and Clinical Pharmacology (12.5)].

3.DOSAGE FORMS AND STRENGTHS

Capsules: 50 mg, 100 mg, 200 mg and 400 mg

4.CONTRAINDICATIONS

CELEBREX is contraindicated:

- In patients with known hypersensitivity to celecoxib, aspirin, or other NSAIDs.
- In patients who have demonstrated allergic-type reactions to sulfonamides.
- In patients who have experienced asthma, urticaria, or allergic-type reactions after taking aspirin or other NSAIDs. Severe anaphylactoid reactions to NSAIDs, some of them fatal, have been reported in such patients [see Warnings and Precautions (5.7, 5.13)].
- For the treatment of peri-operative pain in the setting of coronary artery bypass graft (CABG) surgery [see Warnings and Precautions (5.1)].
- In patients with active gastrointestinal bleeding. [see Warnings and Precautions (5.4)].

5.WARNINGS AND PRECAUTIONS

5.1Cardiovascular Thrombotic Events

Chronic use of CELEBREX may cause an increased risk of serious adverse cardiovascular thrombotic events, myocardial infarction, and stroke, which can be fatal. In the APC (Adenoma Prevention with Celecoxib) trial, the hazard ratio for the composite endpoint of cardiovascular death, MI, or stroke was 3.4 (95% CI 1.4 – 8.5) for CELEBREX 400 mg twice daily and 2.8 (95% CI 1.1 – 7.2) with CELEBREX 200 mg twice daily compared to placebo. Cumulative rates for this composite endpoint over 3 years were 3.0% (20/671 subjects) and 2.5% (17/685 subjects), respectively, compared to 0.9% (6/679 subjects) with placebo treatment. The increases in both celecoxib dose groups versus placebo-treated patients were mainly due to an increased incidence of myocardial infarction [ see Clinical Studies (14.6) ].

All NSAIDs, both COX-2 selective and non-selective, may have a similar risk. Patients with known CV disease or risk factors for CV disease may be at greater risk. To minimize the potential risk for an adverse CV event in patients treated with CELEBREX, the lowest effective dose should be used for the shortest duration consistent with individual patient treatment goals. Physicians and patients should remain alert for the development of such events, even in the absence of previous CV symptoms. Patients should be informed about the signs and/or symptoms of serious CV toxicity and the steps to take if they occur.

There is no consistent evidence that concurrent use of aspirin mitigates the increased risk of serious CV thrombotic events associated with NSAID use. The concurrent use of aspirin and CELEBREX does increase the risk of serious GI events [see Warnings and Precautions (5.4)].

Two large, controlled, clinical trials of a different COX-2 selective NSAID for the treatment of pain in the first 10–14 days following CABG surgery found an increased incidence of myocardial infarction and stroke [see Contraindications (4)].

5.2Hypertension

As with all NSAIDs, CELEBREX can lead to the onset of new hypertension or worsening of preexisting hypertension, either of which may contribute to the increased incidence of CV events. Patients taking thiazides or loop diuretics may have impaired response to these therapies when taking NSAIDs. NSAIDs, including CELEBREX, should be used with caution in patients with hypertension. Blood pressure should be monitored closely during the initiation of therapy with CELEBREX and throughout the course of therapy. The rates of hypertension from the CLASS trial in the CELEBREX, ibuprofen and diclofenac-treated patients were 2.4%, 4.2% and 2.5%, respectively [see Clinical Studies (14.6)].

5.3Congestive Heart Failure and Edema

Fluid retention and edema have been observed in some patients taking NSAIDs, including CELEBREX [see Adverse Reactions (6.1)]. In the CLASS study [see Clinical Studies (14.6)], the Kaplan-Meier cumulative rates at 9 months of peripheral edema in patients on CELEBREX 400 mg twice daily (4-fold and 2-fold the recommended OA and RA doses, respectively), ibuprofen 800 mg three times daily and diclofenac 75 mg twice daily were 4.5%, 6.9% and 4.7%, respectively. CELEBREX should be used with caution in patients with fluid retention or heart failure.

5.4Gastrointestinal (GI) Effects

Risk of GI Ulceration, Bleeding, and Perforation

NSAIDs, including CELEBREX, can cause serious gastrointestinal events including bleeding, ulceration, and perforation of the stomach, small intestine or large intestine, which can be fatal. These serious adverse events can occur at any time, with or without warning symptoms, in patients treated with NSAIDs. Only one in five patients who develop a serious upper GI adverse event on NSAID therapy is symptomatic. Complicated and symptomatic ulcer rates were 0.78% at nine months for all patients in the CLASS trial, and 2.19% for the subgroup on low-dose ASA. Patients 65 years of age and older had an incidence of 1.40% at nine months, 3.06% when also taking ASA [see Clinical Studies (14.6)]. With longer duration of use of NSAIDs, there is a trend for increasing the likelihood of developing a serious GI event at some time during the course of therapy. However, even short-term therapy is not without risk.

NSAIDs should be prescribed with extreme caution in patients with a prior history of ulcer disease or gastrointestinal bleeding. Patients with a prior history of peptic ulcer disease and/or gastrointestinal bleeding who use NSAIDs have a greater than 10-fold increased risk for developing a GI bleed compared to patients with neither of these risk factors. Other factors that increase the risk of GI bleeding in patients treated with NSAIDs include concomitant use of oral corticosteroids or anticoagulants, longer duration of NSAID therapy, smoking, use of alcohol, older age, and poor general health status. Most spontaneous reports of fatal GI events are in elderly or debilitated patients and therefore special care should be taken in treating this population.

To minimize the potential risk for an adverse GI event, the lowest effective dose should be used for the shortest duration consistent with individual patient treatment goals. Physicians and patients should remain alert for signs and symptoms of GI ulceration and bleeding during CELEBREX therapy and promptly initiate additional evaluation and treatment if a serious GI adverse event is suspected. For high-risk patients, alternate therapies that do not involve NSAIDs should be considered.

Celebrex is contraindicated in patients with active GI bleeding.

5.5Hepatic Effects

Borderline elevations of one or more liver-associated enzymes may occur in up to 15% of patients taking NSAIDs, and notable elevations of ALT or AST (approximately 3 or more times the upper limit of normal) have been reported in approximately 1% of patients in clinical trials with NSAIDs. These laboratory abnormalities may progress, may remain unchanged, or may be transient with continuing therapy. Rare cases of severe hepatic reactions, including jaundice and fatal fulminant hepatitis, liver necrosis and hepatic failure (some with fatal outcome) have been reported with NSAIDs, including CELEBREX [see Adverse Reactions (6.1)]. In controlled clinical trials of CELEBREX, the incidence of borderline elevations (greater than or equal to 1.2 times and less than 3 times the upper limit of normal) of liver associated enzymes was 6% for CELEBREX and 5% for placebo, and approximately 0.2% of patients taking CELEBREX and 0.3% of patients taking placebo had notable elevations of ALT and AST.

A patient with symptoms and/or signs suggesting liver dysfunction, or in whom an abnormal liver test has occurred, should be monitored carefully for evidence of the development of a more severe hepatic reaction while on therapy with CELEBREX. If clinical signs and symptoms consistent with liver disease develop, or if systemic manifestations occur (e.g., eosinophilia, rash, etc.), CELEBREX should be discontinued.

5.6Renal Effects

Long-term administration of NSAIDs has resulted in renal papillary necrosis and other renal injury. Renal toxicity has also been seen in patients in whom renal prostaglandins have a compensatory role in the maintenance of renal perfusion. In these patients, administration of an NSAID may cause a dose-dependent reduction in prostaglandin formation and, secondarily, in renal blood flow, which may precipitate overt renal decompensation. Patients at greatest risk of this reaction are those with impaired renal function, heart failure, liver dysfunction, those taking diuretics, ACE-inhibitors, angiotensin II receptor antagonists, and the elderly. Discontinuation of NSAID therapy is usually followed by recovery to the pretreatment state. Clinical trials with CELEBREX have shown renal effects similar to those observed with comparator NSAIDs.

No information is available from controlled clinical studies regarding the use of CELEBREX in patients with advanced renal disease. Therefore, treatment with CELEBREX is not recommended in these patients with advanced renal disease. If CELEBREX therapy must be initiated, close monitoring of the patient's renal function is advisable.

5.7Anaphylactoid Reactions

As with NSAIDs in general, anaphylactoid reactions have occurred in patients without known prior exposure to CELEBREX. In post-marketing experience, rare cases of anaphylactic reactions and angioedema have been reported in patients receiving CELEBREX. CELEBREX should not be given to patients with the aspirin triad. This symptom complex typically occurs in asthmatic patients who experience rhinitis with or without nasal polyps, or who exhibit severe, potentially fatal bronchospasm after taking aspirin or other NSAIDs [see Contraindications (4), Warnings and Precautions (5.7)]. Emergency help should be sought in cases where an anaphylactoid reaction occurs.

5.8Skin Reactions

CELEBREX is a sulfonamide and can cause serious skin adverse events such as exfoliative dermatitis, Stevens-Johnson syndrome (SJS), and toxic epidermal necrolysis (TEN), which can be fatal. These serious events can occur without warning and in patients without prior known sulfa allergy. Patients should be informed about the signs and symptoms of serious skin manifestations and use of the drug should be discontinued at the first appearance of skin rash or any other sign of hypersensitivity.

5.9Pregnancy

In late pregnancy, starting at 30 weeks gestation, CELEBREX should be avoided because it may cause premature closure of the ductus arteriosus [see Use in Specific Populations (8.1)].

5.10 Corticosteroid Treatment

CELEBREX cannot be expected to substitute for corticosteroids or to treat corticosteroid insufficiency. Abrupt discontinuation of corticosteroids may lead to exacerbation of corticosteroid-responsive illness. Patients on prolonged corticosteroid therapy should have their therapy tapered slowly if a decision is made to discontinue corticosteroids.

5.11 Hematological Effects

Anemia is sometimes seen in patients receiving CELEBREX. In controlled clinical trials the incidence of anemia was 0.6% with CELEBREX and 0.4% with placebo. Patients on long-term treatment with CELEBREX should have their hemoglobin or hematocrit checked if they exhibit any signs or symptoms of anemia or blood loss. CELEBREX does not generally affect platelet counts, prothrombin time (PT), or partial thromboplastin time (PTT), and does not inhibit platelet aggregation at indicated dosages [see Clinical Pharmacology (12.2)].

5.12 Disseminated Intravascular Coagulation (DIC)

CELEBREX should be used only with caution in pediatric patients with systemic onset JRA due to the risk of disseminated intravascular coagulation.

5.13 Preexisting Asthma

Patients with asthma may have aspirin-sensitive asthma. The use of aspirin in patients with aspirin-sensitive asthma has been associated with severe bronchospasm, which can be fatal. Since cross reactivity, including bronchospasm, between aspirin and other nonsteroidal anti-inflammatory drugs has been reported in such aspirin-sensitive patients, CELEBREX should not be administered to patients with this form of aspirin sensitivity and should be used with caution in patients with preexisting asthma.

5.14 Laboratory Tests

Because serious GI tract ulcerations and bleeding can occur without warning symptoms, physicians should monitor for signs or symptoms of GI bleeding. Patients on long-term treatment with NSAIDs should have a CBC and a chemistry profile checked periodically. If abnormal liver tests or renal tests persist or worsen, CELEBREX should be discontinued.

In controlled clinical trials, elevated BUN occurred more frequently in patients receiving CELEBREX compared with patients on placebo. This laboratory abnormality was also seen in patients who received comparator NSAIDs in these studies. The clinical significance of this abnormality has not been established.

5.15 Inflammation

The pharmacological activity of CELEBREX in reducing inflammation, and possibly fever, may diminish the utility of these diagnostic signs in detecting infectious complications of presumed noninfectious, painful conditions.

5.16 Concomitant NSAID Use

The concomitant use of CELEBREX with any dose of a non-aspirin NSAID should be avoided due to the potential for increased risk of adverse reactions.

6.ADVERSE REACTIONS

Of the CELEBREX-treated patients in the pre-marketing controlled clinical trials, approximately 4,250 were patients with OA, approximately 2,100 were patients with RA, and approximately 1,050 were patients with post-surgical pain. More than 8,500 patients received a total daily dose of CELEBREX of 200 mg (100 mg twice daily or 200 mg once daily) or more, including more than 400 treated at 800 mg (400 mg twice daily). Approximately 3,900 patients received CELEBREX at these doses for 6 months or more; approximately 2,300 of these have received it for 1 year or more and 124 of these have received it for 2 years or more.

Because clinical trials are conducted under widely varying conditions, adverse reaction rates observed in the clinical trials of a drug cannot be directly compared to rates in the clinical trials of another drug and may not reflect the rates observed in practice. The adverse reaction information from clinical trials does, however, provide a basis for identifying the adverse events that appear to be related to drug use and for approximating rates.

6.1 Pre-marketing Controlled Arthritis Trials

Table 1 lists all adverse events, regardless of causality, occurring in ≥2% of patients receiving CELEBREX from 12 controlled studies conducted in patients with OA or RA that included a placebo and/or a positive control group. Since these 12 trials were of different durations, and patients in the trials may not have been exposed for the same duration of time, these percentages do not capture cumulative rates of occurrence.

Table 1: Adverse Events Occurring in ≥2% of CELEBREX Patients from Pre-marketing Controlled Arthritis Trials
 | CBX N=4146 | Placebo N=1864 | NAP N=1366 | DCF N=387 | IBU N=345
Gastrointestinal
Abdominal Pain | 4.1% | 2.8% | 7.7% | 9.0% | 9.0%
Diarrhea | 5.6% | 3.8% | 5.3% | 9.3% | 5.8%
Dyspepsia | 8.8% | 6.2% | 12.2% | 10.9% | 12.8%
Flatulence | 2.2% | 1.0% | 3.6% | 4.1% | 3.5%
Nausea | 3.5% | 4.2% | 6.0% | 3.4% | 6.7%
Body as a whole
Back Pain | 2.8% | 3.6% | 2.2% | 2.6% | 0.9%
Peripheral Edema | 2.1% | 1.1% | 2.1% | 1.0% | 3.5%
Injury-Accidental | 2.9% | 2.3% | 3.0% | 2.6% | 3.2%
Central, Peripheral Nervous system
Dizziness | 2.0% | 1.7% | 2.6% | 1.3% | 2.3%
Headache | 15.8% | 20.2% | 14.5% | 15.5% | 15.4%
Psychiatric
Insomnia | 2.3% | 2.3% | 2.9% | 1.3% | 1.4%
Respiratory
Pharyngitis | 2.3% | 1.1% | 1.7% | 1.6% | 2.6%
Rhinitis | 2.0% | 1.3% | 2.4% | 2.3% | 0.6%
Sinusitis | 5.0% | 4.3% | 4.0% | 5.4% | 5.8%
Upper Respiratory Infection | 8.1% | 6.7% | 9.9% | 9.8% | 9.9%
Skin
Rash | 2.2% | 2.1% | 2.1% | 1.3% | 1.2%
CBX = CELEBREX 100 – 200 mg twice daily or 200 mg once daily;
NAP = Naproxen 500 mg twice daily;
DCF = Diclofenac 75 mg twice daily;
IBU = Ibuprofen 800 mg three times daily.

In placebo- or active-controlled clinical trials, the discontinuation rate due to adverse events was 7.1% for patients receiving CELEBREX and 6.1% for patients receiving placebo. Among the most common reasons for discontinuation due to adverse events in the CELEBREX treatment groups were dyspepsia and abdominal pain (cited as reasons for discontinuation in 0.8% and 0.7% of CELEBREX patients, respectively). Among patients receiving placebo, 0.6% discontinued due to dyspepsia and 0.6% withdrew due to abdominal pain.

The following adverse reactions occurred in 0.1 – 1.9% of patients treated with CELEBREX (100 – 200 mg twice daily or 200 mg once daily):

Gastrointestinal: | Constipation, diverticulitis, dysphagia, eructation, esophagitis, gastritis, gastroenteritis, gastroesophageal reflux, hemorrhoids, hiatal hernia, melena, dry mouth, stomatitis, tenesmus, vomiting
Cardiovascular: | Aggravated hypertension, angina pectoris, coronary artery disorder, myocardial infarction
General: | Allergy aggravated, allergic reaction, chest pain, cyst NOS, edema generalized, face edema, fatigue, fever, hot flushes, influenza-like symptoms, pain, peripheral pain
Central, peripheral nervous system: | Leg cramps, hypertonia, hypoesthesia, migraine, paresthesia, vertigo
Hearing and vestibular: | Deafness, tinnitus
Heart rate and rhythm: | Palpitation, tachycardia
Liver and biliary: | Hepatic function abnormal, SGOT increased, SGPT increased
Metabolic and nutritional: | BUN increased, CPK increased, hypercholesterolemia, hyperglycemia, hypokalemia, NPN increased, creatinine increased, alkaline phosphatase increased, weight increased
Musculoskeletal: | Arthralgia, arthrosis, myalgia, synovitis, tendinitis
Platelets (bleeding or clotting): | Ecchymosis, epistaxis, thrombocythemia
Psychiatric: | Anorexia, anxiety, appetite increased, depression, nervousness, somnolence
Hemic: | Anemia
Respiratory: | Bronchitis, bronchospasm, bronchospasm aggravated, coughing, dyspnea, laryngitis, pneumonia
Skin and appendages: | Alopecia, dermatitis, photosensitivity reaction, pruritus, rash erythematous, rash maculopapular, skin disorder, skin dry, sweating increased, urticaria
Application site disorders: | Cellulitis, dermatitis contact
Urinary: | Albuminuria, cystitis, dysuria, hematuria, micturition frequency, renal calculus

The following serious adverse events (causality not evaluated) occurred in <0.1% of patients (cases reported only in post-marketing experience are indicated in italics):

Cardiovascular: | Syncope, congestive heart failure, ventricular fibrillation, pulmonary embolism, cerebrovascular accident, peripheral gangrene, thrombophlebitis, vasculitis, deep venous thrombosis
Gastrointestinal: | Intestinal obstruction, intestinal perforation, gastrointestinal bleeding, colitis with bleeding, esophageal perforation, pancreatitis, ileus
Liver and biliary: | Cholelithiasis, hepatitis, jaundice, liver failure
Hemic and lymphatic: | Thrombocytopenia, agranulocytosis,aplastic anemia, pancytopenia, leucopenia
Metabolic: | Hypoglycemia, hyponatremia
Nervous: | Ataxia, suicide, aseptic meningitis, ageusia, anosmia, fatal intracranial hemorrhage [see Drug Interactions (7.1)]
Renal: | Acute renal failure, interstitial nephritis
Skin: | Erythema multiforme, exfoliative dermatitis, Stevens-Johnson syndrome, toxic epidermal necrolysis drug rash with eosinophilia and systemic symptoms (DRESS, or hypersensitivity syndrome)
General: | Sepsis, sudden death, anaphylactoid reaction, angioedema

6.2 The Celecoxib Long-Term Arthritis Safety Study

[see Special Studies (14.6)]

Hematological Events: The incidence of clinically significant decreases in hemoglobin (>2 g/dL) was lower in patients on CELEBREX 400 mg twice daily (0.5%) compared to patients on either diclofenac 75 mg twice daily (1.3%) or ibuprofen 800 mg three times daily 1.9%. The lower incidence of events with CELEBREX was maintained with or without ASA use [see Clinical Pharmacology (12.2)].

Withdrawals/Serious Adverse Events: Kaplan-Meier cumulative rates at 9 months for withdrawals due to adverse events for CELEBREX, diclofenac and ibuprofen were 24%, 29%, and 26%, respectively. Rates for serious adverse events (i.e., causing hospitalization or felt to be life-threatening or otherwise medically significant), regardless of causality, were not different across treatment groups (8%, 7%, and 8%, respectively).

6.3 Juvenile Rheumatoid Arthritis Study

In a 12-week, double-blind, active-controlled study, 242 JRA patients 2 years to 17 years of age were treated with celecoxib or naproxen; 77 JRA patients were treated with celecoxib 3 mg/kg BID, 82 patients were treated with celecoxib 6 mg/kg BID, and 83 patients were treated with naproxen 7.5 mg/kg BID. The most commonly occurring (≥5%) adverse events in celecoxib treated patients were headache, fever (pyrexia), upper abdominal pain, cough, nasopharyngitis, abdominal pain, nausea, arthralgia, diarrhea and vomiting. The most commonly occurring (≥5%) adverse experiences for naproxen-treated patients were headache, nausea, vomiting, fever, upper abdominal pain, diarrhea, cough, abdominal pain, and dizziness (Table 2). Compared with naproxen, celecoxib at doses of 3 and 6 mg/kg BID had no observable deleterious effect on growth and development during the course of the 12-week double-blind study. There was no substantial difference in the number of clinical exacerbations of uveitis or systemic features of JRA among treatment groups.

In a 12-week, open-label extension of the double-blind study described above, 202 JRA patients were treated with celecoxib 6 mg/kg BID. The incidence of adverse events was similar to that observed during the double-blind study; no unexpected adverse events of clinical importance emerged.

Table 2: Adverse Events Occurring in ≥5% of JRA Patients in Any Treatment Group, by System Organ Class (% of patients with events)
 | All Doses Twice Daily
System Organ Class Preferred Term | Celecoxib 3 mg/kg N=77 | Celecoxib 6 mg/kg N=82 | Naproxen 7.5 mg/kg N=83
Any Event | 64 | 70 | 72
Eye Disorders | 5 | 5 | 5
Gastrointestinal | 26 | 24 | 36
Abdominal pain NOS | 4 | 7 | 7
Abdominal pain upper | 8 | 6 | 10
Vomiting NOS | 3 | 6 | 11
Diarrhea NOS | 5 | 4 | 8
Nausea | 7 | 4 | 11
General | 13 | 11 | 18
Pyrexia | 8 | 9 | 11
Infections | 25 | 20 | 27
Nasopharyngitis | 5 | 6 | 5
Injury and Poisoning | 4 | 6 | 5
Investigations [Abnormal laboratory tests, which include: Prolonged activated partial thromboplastin time, Bacteriuria NOS present, Blood creatine phosphokinase increased, Blood culture positive, Blood glucose increased, Blood pressure increased, Blood uric acid increased, Hematocrit decreased, Hematuria present, Hemoglobin decreased, Liver function tests NOS abnormal, Proteinuria present, Transaminase NOS increased, Urine analysis abnormal NOS] | 3 | 11 | 7
Musculoskeletal | 8 | 10 | 17
Arthralgia | 3 | 7 | 4
Nervous System | 17 | 11 | 21
Headache NOS | 13 | 10 | 16
Dizziness (excl vertigo) | 1 | 1 | 7
Respiratory | 8 | 15 | 15
Cough | 7 | 7 | 8
Skin & Subcutaneous | 10 | 7 | 18

6.4 Other Pre-Approval Studies

Adverse Events from Ankylosing Spondylitis Studies: A total of 378 patients were treated with CELEBREX in placebo- and active-controlled AS studies. Doses up to 400 mg once daily were studied. The types of adverse events reported in the AS studies were similar to those reported in the OA/RAstudies.

Adverse Events from Analgesia and Dysmenorrhea Studies: Approximately 1,700 patients were treated with CELEBREX in analgesia and dysmenorrhea studies. All patients in post-oral surgery pain studies received a single dose of study medication. Doses up to 600 mg/day of CELEBREX were studied in primary dysmenorrhea and post-orthopedic surgery pain studies. The types of adverse events in the analgesia and dysmenorrhea studies were similar to those reported in arthritis studies. The only additional adverse event reported was post-dental extraction alveolar osteitis (dry socket) in the post-oral surgery pain studies.

6.5 The APC and PreSAP Trials

Adverse reactions from long-term, placebo-controlled polyp prevention studies: Exposure to CELEBREX in the APC and PreSAP trials was 400 to 800 mg daily for up to 3 years [see Special Studies Adenomatous Polyp Prevention Studies (14.6)].

Some adverse reactions occurred in higher percentages of patients than in the arthritis pre-marketing trials (treatment durations up to 12 weeks; see Adverse events from CELEBREX pre-marketing controlled arthritis trials, above). The adverse reactions for which these differences in patients treated with CELEBREX were greater as compared to the arthritis pre-marketing trials were as follows:

 | CELEBREX (400 to 800 mg daily) N = 2285 | Placebo N=1303
Diarrhea | 10.5% | 7.0%
Gastroesophageal reflux disease | 4.7% | 3.1%
Nausea | 6.8% | 5.3%
Vomiting | 3.2% | 2.1%
Dyspnea | 2.8% | 1.6%
Hypertension | 12.5% | 9.8%

The following additional adverse reactions occurred in ≥0.1% and <1% of patients taking CELEBREX, at an incidence greater than placebo in the long-term polyp prevention studies and were either not reported during the controlled arthritis pre-marketing trials or occurred with greater frequency in the long-term, placebo-controlled polyp prevention studies:

Nervous system disorders: | Cerebral infarction
Eye disorders: | Vitreous floaters, conjunctival hemorrhage
Ear and labyrinth: | Labyrinthitis
Cardiac disorders: | Angina unstable, aortic valve incompetence, coronary artery atherosclerosis, sinus bradycardia, ventricular hypertrophy
Vascular disorders: | Deep vein thrombosis
Reproductive system and breast disorders: | Ovarian cyst
Investigations: | Blood potassium increased, blood sodium increased, blood testosterone decreased
Injury, poisoning and procedural complications: | Epicondylitis, tendon rupture

7.DRUG INTERACTIONS

General: Celecoxib metabolism is predominantly mediated via cytochrome P450 (CYP) 2C9 in the liver. Co-administration of celecoxib with drugs that are known to inhibit CYP2C9 should be done with caution. Significant interactions may occur when celecoxib is administered together with drugs that inhibit CYP2C9.

In vitro studies indicate that celecoxib, although not a substrate, is an inhibitor of CYP2D6. Therefore, there is a potential for an in vivo drug interaction with drugs that are metabolized by CYP2D6.

7.1Warfarin

Anticoagulant activity should be monitored, particularly in the first few days, after initiating or changing CELEBREX therapy in patients receiving warfarin or similar agents, since these patients are at an increased risk of bleeding complications. The effect of celecoxib on the anticoagulant effect of warfarin was studied in a group of healthy subjects receiving daily 2–5 mg doses of warfarin. In these subjects, celecoxib did not alter the anticoagulant effect of warfarin as determined by prothrombin time. However, in post-marketing experience, serious bleeding events, some of which were fatal, have been reported, predominantly in the elderly, in association with increases in prothrombin time in patients receiving CELEBREX concurrently with warfarin.

7.2Lithium

In a study conducted in healthy subjects, mean steady-state lithium plasma levels increased approximately 17% in subjects receiving lithium 450 mg twice daily with CELEBREX 200 mg twice daily as compared to subjects receiving lithium alone. Patients on lithium treatment should be closely monitored when CELEBREX is introduced or withdrawn.

7.3Aspirin

CELEBREX can be used with low-dose aspirin. However, concomitant administration of aspirin with CELEBREX increases the rate of GI ulceration or other complications, compared to use of CELEBREX alone [see Warnings and Precautions (5.1, 5.4) and Clinical Studies (14.6)]. Because of its lack of platelet effects, CELEBREX is not a substitute for aspirin for cardiovascular prophylaxis [see Clinical Pharmacology (12.2)].

7.4ACE-inhibitors and Angiotensin II Antagonists

Reports suggest that NSAIDs may diminish the antihypertensive effect of Angiotensin Converting Enzyme (ACE) inhibitors and angiotensin II antagonists. This interaction should be given consideration in patients taking CELEBREX concomitantly with ACE-inhibitors and angiotensin II antagonists [see Clinical Pharmacology (12.2].

In patients who are elderly, volume-depleted (including those on diuretic therapy), or with compromised renal function, co-administration of NSAIDs, including selective COX-2 inhibitors, with ACE inhibitors, may result in deterioration of renal function, including possible acute renal failure. Discontinuation of NSAID therapy is usually followed by recovery to the pretreatment state.

7.5Fluconazole

Concomitant administration of fluconazole at 200 mg once daily resulted in a two-fold increase in celecoxib plasma concentration. This increase is due to the inhibition of celecoxib metabolism via P450 2C9 by fluconazole [see Clinical Pharmacology (12.3)]. CELEBREX should be introduced at the lowest recommended dose in patients receiving fluconazole.

7.6Furosemide

Clinical studies, as well as post-marketing observations, have shown that NSAIDs can reduce the natriuretic effect of furosemide and thiazides in some patients. This response has been attributed to inhibition of renal prostaglandin synthesis.

7.7 Methotrexate

In an interaction study of rheumatoid arthritis patients taking methotrexate, CELEBREX did not have an effect on the pharmacokinetics of methotrexate [see Clinical Pharmacology (12.3)].

7.8 Concomitant NSAID Use

The concomitant use of CELEBREX with any dose of a non-aspirin NSAID should be avoided due to the potential for increased risk of adverse reactions.

8.USE IN SPECIFIC POPULATIONS

8.1Pregnancy

Pregnancy Category C. Pregnancy category D from 30 weeks of gestation onward.

TERATOGENIC EFFECTS

Teratogenic effects: Celecoxib at oral doses ≥150 mg/kg/day (approximately 2-fold human exposure at 200 mg twice daily as measured by AUC0–24), caused an increased incidence of ventricular septal defects, a rare event, and fetal alterations, such as ribs fused, sternebrae fused and sternebrae misshapen when rabbits were treated throughout organogenesis. A dose-dependent increase in diaphragmatic hernias was observed when rats were given celecoxib at oral doses ≥30 mg/kg/day (approximately 6-fold human exposure based on the AUC0–24 at 200 mg twice daily) throughout organogenesis. There are no studies in pregnant women. CELEBREX should be used during pregnancy only if the potential benefit justifies the potential risk to the fetus.

NONTERATOGENIC EFFECTS

Nonteratogenic effects: Celecoxib produced pre-implantation and post-implantation losses and reduced embryo/fetal survival in rats at oral dosages ≥50 mg/kg/day (approximately 6-fold human exposure based on the AUC0–24 at 200 mg twice daily). These changes are expected with inhibition of prostaglandin synthesis and are not the result of permanent alteration of female reproductive function, nor are they expected at clinical exposures. No studies have been conducted to evaluate the effect of celecoxib on the closure of the ductus arteriosus in humans. Therefore, use of CELEBREX during the third trimester of pregnancy should be avoided.

8.2Labor and Delivery

Celecoxib produced no evidence of delayed labor or parturition at oral doses up to 100 mg/kg in rats (approximately 7-fold human exposure as measured by the AUC0–24 at 200 mg BID). The effects of CELEBREX on labor and delivery in pregnant women are unknown.

8.3Nursing Mothers

Limited data from 3 published reports that included a total of 12 breastfeeding women showed low levels of CELEBREX in breast milk. The calculated average daily infant dose was 10–40 mcg/kg/day, less than 1% of the weight-based therapeutic dose for a two-year old-child. A report of two breastfed infants 17 and 22 months of age did not show any adverse events. Caution should be exercised when CELEBREX is administered to a nursing woman.

8.4Pediatric Use

CELEBREX is approved for relief of the signs and symptoms of Juvenile Rheumatoid Arthritis in patients 2 years and older. Safety and efficacy have not been studied beyond six months in children. The long-term cardiovascular toxicity in children exposed to CELEBREX has not been evaluated and it is unknown if long-term risks may be similar to that seen in adults exposed to CELEBREX or other COX-2 selective and non-selective NSAIDs [(see Boxed Warning, Warnings and Precautions (5.12), and Clinical Studies (14.3)].

The use of celecoxib in patients 2 years to 17 years of age with pauciarticular, polyarticular course JRA or in patients with systemic onset JRA was studied in a 12-week, double-blind, active controlled, pharmacokinetic, safety and efficacy study, with a 12-week open-label extension. Celecoxib has not been studied in patients under the age of 2 years, in patients with body weight less than 10 kg (22 lbs), and in patients with active systemic features. Patients with systemic onset JRA (without active systemic features) appear to be at risk for the development of abnormal coagulation laboratory tests. In some patients with systemic onset JRA, both celecoxib and naproxen were associated with mild prolongation of activated partial thromboplastin time (APTT) but not prothrombin time (PT). NSAIDs including celecoxib should be used only with caution in patients with systemic onset JRA, due to the risk of disseminated intravascular coagulation. Patients with systemic onset JRA should be monitored for the development of abnormal coagulation tests [see Dosage and Administration (2.3), Warnings and Precautions (5.12), Adverse Reactions (6.3), Animal Toxicology (13.2), Clinical Studies (14.3)].

Alternative therapies for treatment of JRA should be considered in pediatric patients identified to be CYP2C9 poor metabolizers [see Poor Metabolizers of CYP2C9 substrates (8.8)].

8.5Geriatric Use

Of the total number of patients who received CELEBREX in pre-approval clinical trials, more than 3,300 were 65–74 years of age, while approximately 1,300 additional patients were 75 years and over. No substantial differences in effectiveness were observed between these subjects and younger subjects. In clinical studies comparing renal function as measured by the GFR, BUN and creatinine, and platelet function as measured by bleeding time and platelet aggregation, the results were not different between elderly and young volunteers. However, as with other NSAIDs, including those that selectively inhibit COX-2, there have been more spontaneous post-marketing reports of fatal GI events and acute renal failure in the elderly than in younger patients [see Warnings and Precautions (5.4, 5.6)].

8.6 Hepatic Insufficiency

The daily recommended dose of CELEBREX capsules in patients with moderate hepatic impairment (Child-Pugh Class B) should be reduced by 50%. The use of CELEBREX in patients with severe hepatic impairment is not recommended [see Dosage and Administration (2.6) and Clinical Pharmacology (12.3)].

8.7 Renal Insufficiency

CELEBREX is not recommended in patients with severe renal insufficiency [see Warnings and Precautions (5.6) and Clinical Pharmacology (12.3)].

8.8 Poor Metabolizers of CYP2C9 Substrates

Patients who are known or suspected to be poor CYP2C9 metabolizers based on genotype or previous history/experience with other CYP2C9 substrates (such as warfarin, phenytoin) should be administered celecoxib with caution. Consider starting treatment at half the lowest recommended dose in poor metabolizers (i.e., CYP2C9*3/*3). Alternative management should be considered in JRA patients identified to be CYP2C9 poor metabolizers. [see Dosage and Administration (2.6) and Clinical Pharmacology (12.5)].

10.OVERDOSAGE

No overdoses of CELEBREX were reported during clinical trials. Doses up to 2400 mg/day for up to 10 days in 12 patients did not result in serious toxicity. Symptoms following acute NSAID overdoses are usually limited to lethargy, drowsiness, nausea, vomiting, and epigastric pain, which are generally reversible with supportive care. Gastrointestinal bleeding can occur. Hypertension, acute renal failure, respiratory depression and coma may occur, but are rare. Anaphylactoid reactions have been reported with therapeutic ingestion of NSAIDs, and may occur following an overdose.

Patients should be managed by symptomatic and supportive care following an NSAID overdose. There are no specific antidotes. No information is available regarding the removal of celecoxib by hemodialysis, but based on its high degree of plasma protein binding (>97%) dialysis is unlikely to be useful in overdose. Emesis and/or activated charcoal (60 to 100 g in adults, 1 to 2 g/kg in children) and/or osmotic cathartic may be indicated in patients seen within 4 hours of ingestion with symptoms or following a large overdose. Forced diuresis, alkalinization of urine, hemodialysis, or hemoperfusion may not be useful due to high protein binding.

11.DESCRIPTION

CELEBREX (celecoxib) is chemically designated as 4-[5-(4-methylphenyl)- 3-(trifluoromethyl)-1H-pyrazol-1-yl] benzenesulfonamide and is a diaryl-substituted pyrazole. The empirical formula is C17H14F3N3O2S, and the molecular weight is 381.38; the chemical structure is as follows:

CELEBREX oral capsules contain either 50 mg, 100 mg, 200 mg or 400 mg of celecoxib, together with inactive ingredients including: croscarmellose sodium, edible inks, gelatin, lactose monohydrate, magnesium stearate, povidone and sodium lauryl sulfate.

12.CLINICAL PHARMACOLOGY

12.1Mechanism of Action

CELEBREX is a nonsteroidal anti-inflammatory drug that exhibits anti-inflammatory, analgesic, and antipyretic activities in animal models. The mechanism of action of CELEBREX is believed to be due to inhibition of prostaglandin synthesis, primarily via inhibition of cyclooxygenase-2 (COX-2), and at therapeutic concentrations in humans, CELEBREX does not inhibit the cyclooxygenase-1 (COX-1) isoenzyme. In animal colon tumor models, CELEBREX reduced the incidence and multiplicity of tumors.

12.2Pharmacodynamics

Platelets: In clinical trials using normal volunteers, CELEBREX at single doses up to 800 mg and multiple doses of 600 mg twice daily for up to 7 days duration (higher than recommended therapeutic doses) had no effect on reduction of platelet aggregation or increase in bleeding time. Because of its lack of platelet effects, CELEBREX is not a substitute for aspirin for cardiovascular prophylaxis. It is not known if there are any effects of CELEBREX on platelets that may contribute to the increased risk of serious cardiovascular thrombotic adverse events associated with the use of CELEBREX.

Fluid Retention: Inhibition of PGE2 synthesis may lead to sodium and water retention through increased reabsorption in the renal medullary thick ascending loop of Henle and perhaps other segments of the distal nephron. In the collecting ducts, PGE2 appears to inhibit water reabsorption by counteracting the action of antidiuretic hormone.

12.3Pharmacokinetics

Absorption: Peak plasma levels of celecoxib occur approximately 3 hrs after an oral dose. Under fasting conditions, both peak plasma levels (Cmax) and area under the curve (AUC) are roughly dose-proportional up to 200 mg BID; at higher doses there are less than proportional increases in Cmax and AUC [see Food Effects]. Absolute bioavailability studies have not been conducted. With multiple dosing, steady-state conditions are reached on or before Day 5. The pharmacokinetic parameters of celecoxib in a group of healthy subjects are shown in Table 3.

Table 3 Summary of Single Dose (200 mg) Disposition Kinetics of Celecoxib in Healthy Subjects [Subjects under fasting conditions (n=36, 19–52 yrs.)]
Mean (%CV) PK Parameter Values
Cmax, ng/mL | Tmax, hr | Effective t1/2, hr | Vss/F, L | CL/F, L/hr
705 (38) | 2.8 (37) | 11.2 (31) | 429 (34) | 27.7 (28)

Food Effects: When CELEBREX capsules were taken with a high fat meal, peak plasma levels were delayed for about 1 to 2 hours with an increase in total absorption (AUC) of 10% to 20%. Under fasting conditions, at doses above 200 mg, there is less than a proportional increase in Cmax and AUC, which is thought to be due to the low solubility of the drug in aqueous media.

Coadministration of CELEBREX with an aluminum- and magnesium-containing antacids resulted in a reduction in plasma celecoxib concentrations with a decrease of 37% in Cmax and 10% in AUC. CELEBREX, at doses up to 200 mg twice daily, can be administered without regard to timing of meals. Higher doses (400 mg twice daily) should be administered with food to improve absorption.

In healthy adult volunteers, the overall systemic exposure (AUC) of celecoxib was equivalent when celecoxib was administered as intact capsule or capsule contents sprinkled on applesauce. There were no significant alterations in Cmax, Tmax or t1/2 after administration of capsule contents on applesauce [see Dosage and Administration (2)].

Distribution: In healthy subjects, celecoxib is highly protein bound (~97%) within the clinical dose range. In vitro studies indicate that celecoxib binds primarily to albumin and, to a lesser extent, α1-acid glycoprotein. The apparent volume of distribution at steady state (Vss/F) is approximately 400 L, suggesting extensive distribution into the tissues. Celecoxib is not preferentially bound to red blood cells.

Metabolism: Celecoxib metabolism is primarily mediated via CYP2C9. Three metabolites, a primary alcohol, the corresponding carboxylic acid and its glucuronide conjugate, have been identified in human plasma. These metabolites are inactive as COX-1 or COX-2 inhibitors.

Excretion: Celecoxib is eliminated predominantly by hepatic metabolism with little (<3%) unchanged drug recovered in the urine and feces. Following a single oral dose of radiolabeled drug, approximately 57% of the dose was excreted in the feces and 27% was excreted into the urine. The primary metabolite in both urine and feces was the carboxylic acid metabolite (73% of dose) with low amounts of the glucuronide also appearing in the urine. It appears that the low solubility of the drug prolongs the absorption process making terminal half-life (t1/2) determinations more variable. The effective half-life is approximately 11 hours under fasted conditions. The apparent plasma clearance (CL/F) is about 500 mL/min.

Geriatric: At steady state, elderly subjects (over 65 years old) had a 40% higher Cmax and a 50% higher AUC compared to the young subjects. In elderly females, celecoxib Cmax and AUC are higher than those for elderly males, but these increases are predominantly due to lower body weight in elderly females. Dose adjustment in the elderly is not generally necessary. However, for patients of less than 50 kg in body weight, initiate therapy at the lowest recommended dose [see Dosage and Administration (2.6) and Use in Specific Populations (8.5)].

Pediatric: The steady state pharmacokinetics of celecoxib administered as an investigational oral suspension was evaluated in 152 JRA patients 2 years to 17 years of age weighing ≥10 kg with pauciarticular or polyarticular course JRA and in patients with systemic onset JRA. Population pharmacokinetic analysis indicated that the oral clearance (unadjusted for body weight) of celecoxib increases less than proportionally to increasing weight, with 10 kg and 25 kg patients predicted to have 40% and 24% lower clearance, respectively, compared with a 70 kg adult RA patient.

Twice-daily administration of 50 mg capsules to JRA patients weighing ≥12 to ≤25 kg and 100 mg capsules to JRA patients weighing >25 kg should achieve plasma concentrations similar to those observed in a clinical trial that demonstrated the non-inferiority of celecoxib to naproxen 7.5 mg/kg twice daily (see Dosage and Administration (2.3). Celecoxib has not been studied in JRA patients under the age of 2 years, in patients with body weight less than 10 kg (22 lbs), or beyond 24 weeks.

Race: Meta-analysis of pharmacokinetic studies has suggested an approximately 40% higher AUC of celecoxib in Blacks compared to Caucasians. The cause and clinical significance of this finding is unknown.

Hepatic Insufficiency: A pharmacokinetic study in subjects with mild (Child-Pugh Class A) and moderate (Child-Pugh Class B) hepatic impairment has shown that steady-state celecoxib AUC is increased about 40% and 180%, respectively, above that seen in healthy control subjects. Therefore, the daily recommended dose of CELEBREX capsules should be reduced by approximately 50% in patients with moderate (Child-Pugh Class B) hepatic impairment. Patients with severe hepatic impairment (Child-Pugh Class C) have not been studied. The use of CELEBREX in patients with severe hepatic impairment is not recommended [see Dosage and Administration (2.6) and Use in Specific Populations (8.6)].

Renal Insufficiency: In a cross-study comparison, celecoxib AUC was approximately 40% lower in patients with chronic renal insufficiency (GFR 35–60 mL/min) than that seen in subjects with normal renal function. No significant relationship was found between GFR and celecoxib clearance. Patients with severe renal insufficiency have not been studied. Similar to other NSAIDs, CELEBREX is not recommended in patients with severe renal insufficiency [see Warnings and Precautions (5.6)].

Drug interactions:

In vitro studies indicate that celecoxib is not an inhibitor of cytochrome P450 2C9, 2C19 or 3A4.

In vivo studies have shown the following:

Lithium: In a study conducted in healthy subjects, mean steady-state lithium plasma levels increased approximately 17% in subjects receiving lithium 450 mg twice daily with CELEBREX 200 mg twice daily as compared to subjects receiving lithium alone [see Drug Interactions (7.2)].

Fluconazole: Concomitant administration of fluconazole at 200 mg once daily resulted in a two-fold increase in celecoxib plasma concentration. This increase is due to the inhibition of celecoxib metabolism via P450 2C9 by fluconazole [see Drug Interactions (7.5)].

Other Drugs: The effects of celecoxib on the pharmacokinetics and/or pharmacodynamics of glyburide, ketoconazole, methotrexate [see Drug Interactions (7.7)], phenytoin, and tolbutamide have been studied in vivo and clinically important interactions have not been found.

12.5 Pharmacogenomics

CYP2C9 activity is reduced in individuals with genetic polymorphisms that lead to reduced enzyme activity, such as those homozygous for the CYP2C9*2 and CYP2C9*3 polymorphisms. Limited data from 4 published reports that included a total of 8 subjects with the homozygous CYP2C9*3/*3 genotype showed celecoxib systemic levels that were 3- to 7-fold higher in these subjects compared to subjects with CYP2C9*1/*1 or *I/*3 genotypes. The pharmacokinetics of celecoxib have not been evaluated in subjects with other CYP2C9 polymorphisms, such as *2, *5, *6, *9 and *11. It is estimated that the frequency of the homozygous *3/*3 genotype is 0.3% to 1.0% in various ethnic groups. [see Dosage and Administration (2.6), Use in Specific Populations (8.8)].

13. NONCLINICAL TOXICOLOGY

13.1 Carcinogenesis, Mutagenesis, Impairment of Fertility

Celecoxib was not carcinogenic in rats given oral doses up to 200 mg/kg for males and 10 mg/kg for females (approximately 2-to 4-fold the human exposure as measured by the AUC0–24 at 200 mg twice daily) or in mice given oral doses up to 25 mg/kg for males and 50 mg/kg for females (approximately equal to human exposure as measured by the AUC0–24 at 200 mg twice daily) for two years.

Celecoxib was not mutagenic in an Ames test and a mutation assay in Chinese hamster ovary (CHO) cells, nor clastogenic in a chromosome aberration assay in CHO cells and an in vivo micronucleus test in rat bone marrow.

Celecoxib did not impair male and female fertility in rats at oral doses up to 600 mg/kg/day (approximately 11-fold human exposure at 200 mg twice daily based on the AUC0–24).

13.2 Animal Toxicology

An increase in the incidence of background findings of spermatocele with or without secondary changes such as epididymal hypospermia as well as minimal to slight dilation of the seminiferous tubules was seen in the juvenile rat. These reproductive findings while apparently treatment-related did not increase in incidence or severity with dose and may indicate an exacerbation of a spontaneous condition. Similar reproductive findings were not observed in studies of juvenile or adult dogs or in adult rats treated with celecoxib. The clinical significance of this observation is unknown.

14.CLINICAL STUDIES

14.1Osteoarthritis

CELEBREX has demonstrated significant reduction in joint pain compared to placebo. CELEBREX was evaluated for treatment of the signs and the symptoms of OA of the knee and hip in placebo- and active-controlled clinical trials of up to 12 weeks duration. In patients with OA, treatment with CELEBREX 100 mg twice daily or 200 mg once daily resulted in improvement in WOMAC (Western Ontario and McMaster Universities) osteoarthritis index, a composite of pain, stiffness, and functional measures in OA. In three 12-week studies of pain accompanying OA flare, CELEBREX doses of 100 mg twice daily and 200 mg twice daily provided significant reduction of pain within 24–48 hours of initiation of dosing. At doses of 100 mg twice daily or 200 mg twice daily the effectiveness of CELEBREX was shown to be similar to that of naproxen 500 mg twice daily. Doses of 200 mg twice daily provided no additional benefit above that seen with 100 mg twice daily. A total daily dose of 200 mg has been shown to be equally effective whether administered as 100 mg twice daily or 200 mg once daily.

14.2Rheumatoid Arthritis

CELEBREX has demonstrated significant reduction in joint tenderness/pain and joint swelling compared to placebo. CELEBREX was evaluated for treatment of the signs and symptoms of RA in placebo- and active-controlled clinical trials of up to 24 weeks in duration. CELEBREX was shown to be superior to placebo in these studies, using the ACR20 Responder Index, a composite of clinical, laboratory, and functional measures in RA. CELEBREX doses of 100 mg twice daily and 200 mg twice daily were similar in effectiveness and both were comparable to naproxen 500 mg twice daily.

Although CELEBREX 100 mg twice daily and 200 mg twice daily provided similar overall effectiveness, some patients derived additional benefit from the 200 mg twice daily dose. Doses of 400 mg twice daily provided no additional benefit above that seen with 100–200 mg twice daily.

14.3Juvenile Rheumatoid Arthritis

In a 12-week, randomized, double-blind active-controlled, parallel-group, multicenter, non-inferiority study, patients from 2 years to 17 years of age with pauciarticular, polyarticular course JRA or systemic onset JRA (with currently inactive systemic features), received one of the following treatments: celecoxib 3 mg/kg (to a maximum of 150 mg) twice daily; celecoxib 6 mg/kg (to a maximum of 300 mg) twice daily; or naproxen 7.5 mg/kg (to a maximum of 500 mg) twice daily. The response rates were based upon the JRA Definition of Improvement greater than or equal to 30% (JRA DOI 30) criterion, which is a composite of clinical, laboratory, and functional measures of JRA. The JRA DOI 30 response rates at week 12 were 69%, 80% and 67% in the celecoxib 3 mg/kg BID, celecoxib 6 mg/kg BID, and naproxen 7.5 mg/kg BID treatment groups, respectively.

The efficacy and safety of CELEBREX for JRA have not been studied beyond six months. The long-term cardiovascular toxicity in children exposed to CELEBREX has not been evaluated and it is unknown if the long-term risk may be similar to that seen in adults exposed to CELEBREX or other COX-2 selective and non-selective NSAIDs [(see Boxed Warning, Warnings and Precautions (5.12)].

14.4Ankylosing Spondylitis

CELEBREX was evaluated in AS patients in two placebo- and active-controlled clinical trials of 6 and 12 weeks duration. CELEBREX at doses of 100 mg twice daily, 200 mg once daily and 400 mg once daily was shown to be statistically superior to placebo in these studies for all three co-primary efficacy measures assessing global pain intensity (Visual Analogue Scale), global disease activity (Visual Analogue Scale) and functional impairment (Bath Ankylosing Spondylitis Functional Index). In the 12-week study, there was no difference in the extent of improvement between the 200 mg and 400 mg CELEBREX doses in a comparison of mean change from baseline, but there was a greater percentage of patients who responded to CELEBREX 400 mg, 53%, than to CELEBREX 200 mg, 44%, using the Assessment in Ankylosing Spondylitis response criteria (ASAS 20). The ASAS 20 defines a responder as improvement from baseline of at least 20% and an absolute improvement of at least 10 mm, on a 0 to 100 mm scale, in at least three of the four following domains: patient global pain, Bath Ankylosing Spondylitis Functional Index, and inflammation. The responder analysis also demonstrated no change in the responder rates beyond 6 weeks.

14.5Analgesia, including Primary Dysmenorrhea

In acute analgesic models of post-oral surgery pain, post-orthopedic surgical pain, and primary dysmenorrhea, CELEBREX relieved pain that was rated by patients as moderate to severe. Single doses [see Dosage and Administration (2.5)] of CELEBREX provided pain relief within 60 minutes.

14.6Special Studies

Adenomatous Polyp Prevention Studies:

Cardiovascular safety was evaluated in two randomized, double-blind, placebo-controlled, three year studies involving patients with Sporadic Adenomatous Polyps treated with CELEBREX: the APC trial (Adenoma Prevention with Celecoxib) and the PreSAP trial (Prevention of Spontaneous Adenomatous Polyps). In the APC trial, there was a dose-related increase in the composite endpoint (adjudicated) of cardiovascular death, myocardial infarction, or stroke with celecoxib compared to placebo over 3 years of treatment. The PreSAP trial did not demonstrate a statistically significant increased risk for the same composite endpoint (adjudicated):

- In the APC trial, the hazard ratios compared to placebo for a composite endpoint (adjudicated) of cardiovascular death, myocardial infarction, or stroke were 3.4 (95% CI 1.4 – 8.5) with celecoxib 400 mg twice daily and 2.8 (95% CI 1.1 – 7.2) with celecoxib 200 mg twice daily. Cumulative rates for this composite endpoint over 3 years were 3.0% (20/671 subjects) and 2.5% (17/685 subjects), respectively, compared to 0.9% (6/679 subjects) with placebo treatment. The increases in both celecoxib dose groups versus placebo-treated patients were mainly due to an increased incidence of myocardial infarction.
- In the PreSAP trial, the hazard ratio for this same composite endpoint (adjudicated) was 1.2 (95% CI 0.6 – 2.4) with celecoxib 400 mg once daily compared to placebo. Cumulative rates for this composite endpoint over 3 years were 2.3% (21/933 subjects) and 1.9% (12/628 subjects), respectively.

Clinical trials of other COX-2 selective and non-selective NSAIDs of up to three-years duration have shown an increased risk of serious cardiovascular thrombotic events, myocardial infarction, and stroke, which can be fatal. As a result, all NSAIDs are considered potentially associated with this risk.

Celecoxib Long-Term Arthritis Safety Study (CLASS):

This was a prospective, long-term, safety outcome study conducted post-marketing in approximately 5,800 OA patients and 2,200 RA patients. Patients received CELEBREX 400 mg twice daily (4-fold and 2-fold the recommended OA and RA doses, respectively), ibuprofen 800 mg three times daily or diclofenac 75 mg twice daily (common therapeutic doses). Median exposures for CELEBREX (n = 3,987) and diclofenac (n = 1,996) were 9 months while ibuprofen (n = 1,985) was 6 months. The primary endpoint of this outcome study was the incidence of complicated ulcers (gastrointestinal bleeding, perforation or obstruction). Patients were allowed to take concomitant low-dose (≤ 325 mg/day) aspirin (ASA) for cardiovascular prophylaxis (ASA subgroups: CELEBREX, n = 882; diclofenac, n = 445; ibuprofen, n = 412). Differences in the incidence of complicated ulcers between CELEBREX and the combined group of ibuprofen and diclofenac were not statistically significant.

Patients on CELEBREX and concomitant low-dose ASA (N=882) experienced 4-fold higher rates of complicated ulcers compared to those not on ASA (N=3105). The Kaplan-Meier rate for complicated ulcers at 9 months was 1.12% versus 0.32% for those on low-dose ASA and those not on ASA, respectively [see Warnings and Precautions (5.4)].

The estimated cumulative rates at 9 months of complicated and symptomatic ulcers for patients treated with CELEBREX 400 mg twice daily are described in Table 4. Table 4 also displays results for patients less than or greater than 65 years of age. The difference in rates between CELEBREX alone and CELEBREX with ASA groups may be due to the higher risk for GI events in ASA users.

Table 4: Complicated and Symptomatic Ulcer Rates in Patients Taking CELEBREX 400 mg Twice Daily (Kaplan-Meier Rates at 9 months [%]) Based on Risk Factors
All Patients
CELEBREX alone (n=3105) | 0.78
CELEBREX with ASA (n=882) | 2.19
Patients <65 Years
CELEBREX alone (n=2025) | 0.47
CELEBREX with ASA (n=403) | 1.26
Patients ≥65 Years
CELEBREX alone (n=1080) | 1.40
CELEBREX with ASA (n=479) | 3.06

In a small number of patients with a history of ulcer disease, the complicated and symptomatic ulcer rates in patients taking CELEBREX alone or CELEBREX with ASA were, respectively, 2.56% (n=243) and 6.85% (n=91) at 48 weeks. These results are to be expected in patients with a prior history of ulcer disease [see Warnings and Precautions (5.4) and Adverse Reactions (6.1)].

Cardiovascular safety outcomes were also evaluated in the CLASS trial. Kaplan-Meier cumulative rates for investigator-reported serious cardiovascular thromboembolic adverse events (including MI, pulmonary embolism, deep venous thrombosis, unstable angina, transient ischemic attacks, and ischemic cerebrovascular accidents) demonstrated no differences between the CELEBREX, diclofenac, or ibuprofen treatment groups. The cumulative rates in all patients at nine months for CELEBREX, diclofenac, and ibuprofen were 1.2%, 1.4%, and 1.1%, respectively. The cumulative rates in non-ASA users at nine months in each of the three treatment groups were less than 1%. The cumulative rates for myocardial infarction in non-ASA users at nine months in each of the three treatment groups were less than 0.2%. There was no placebo group in the CLASS trial, which limits the ability to determine whether the three drugs tested had no increased risk of CV events or if they all increased the risk to a similar degree.

Endoscopic Studies: The correlation between findings of short-term endoscopic studies with CELEBREX and the relative incidence of clinically significant serious upper GI events with long-term use has not been established. Serious clinically significant upper GI bleeding has been observed in patients receiving CELEBREX in controlled and open-labeled trials [see Warnings and Precautions (5.4) and Clinical Studies (14.6)]

A randomized, double-blind study in 430 RA patients was conducted in which an endoscopic examination was performed at 6 months. The incidence of endoscopic ulcers in patients taking CELEBREX 200 mg twice daily was 4% vs. 15% for patients taking diclofenac SR 75 mg twice daily. However, CELEBREX was not statistically different than diclofenac for clinically relevant GI outcomes in the CLASS trial [see Clinical Studies (14.6)].

The incidence of endoscopic ulcers was studied in two 12-week, placebo-controlled studies in 2157 OA and RA patients in whom baseline endoscopies revealed no ulcers. There was no dose relationship for the incidence of gastroduodenal ulcers and the dose of CELEBREX (50 mg to 400 mg twice daily). The incidence for naproxen 500 mg twice daily was 16.2 and 17.6% in the two studies, for placebo was 2.0 and 2.3%, and for all doses of CELEBREX the incidence ranged between 2.7%–5.9%. There have been no large, clinical outcome studies to compare clinically relevant GI outcomes with CELEBREX and naproxen.

In the endoscopic studies, approximately 11% of patients were taking aspirin (≤ 325 mg/day). In the CELEBREX groups, the endoscopic ulcer rate appeared to be higher in aspirin users than in non-users. However, the increased rate of ulcers in these aspirin users was less than the endoscopic ulcer rates observed in the active comparator groups, with or without aspirin.

16.HOW SUPPLIED/STORAGE AND HANDLING

CELEBREX 200 mg capsules are white, with reverse printed white on gold band with markings of 7767 on the cap and 200 on the body, supplied as:

NDC Number Size

63187-079-15 bottle of 15

STORAGE AND HANDLING

Storage: Store at 25°C (77°F); excursions permitted to 15–30°C (59–86°F) [see USP Controlled Room Temperature]

17. PATIENT COUNSELING INFORMATION

Patients should be informed of the following information before initiating therapy with CELEBREX and periodically during the course of ongoing therapy.

17.1Medication Guide

Patients should be informed of the availability of a Medication Guide for NSAIDs that accompanies each prescription dispensed, and should be instructed to read the Medication Guide prior to using CELEBREX.

17.2Cardiovascular Effects

Patients should be informed that CELEBREX may cause serious CV side effects such as MI or stroke, which may result in hospitalization and even death. Patients should be informed of the signs and symptoms of chest pain, shortness of breath, weakness, slurring of speech, and to seek immediate medical advice if they observe any of these signs or symptoms. [see Warnings and Precautions (5.1)].

Patients should be informed that CELEBREX can lead to the onset of new hypertension or worsening of preexisting hypertension, and that CELEBREX may impair the response of some antihypertensive agents. Patients should be instructed on the proper follow up for monitoring of blood pressure. [see Warnings and Precautions (5.2) and Drug Interactions (7.4)].

17.3Gastrointestinal Effects

Patients should be informed that CELEBREX can cause gastrointestinal discomfort and more serious side effects, such as ulcers and bleeding, which may result in hospitalization and even death. Patients should be informed of the signs and symptoms of ulcerations and bleeding, and to seek immediate medical advice if they observe any signs or symptoms that are indicative of these disorders, including epigastric pain, dyspepsia, melena, and hematemesis. [see Warnings and Precautions (5.4)].

17.4Hepatic Effects

Patients should be informed of the warning signs and symptoms of hepatotoxicity (e.g., nausea, fatigue, lethargy, pruritus, jaundice, right upper quadrant tenderness, and "flu-like" symptoms). Patients should be instructed that they should stop therapy and seek immediate medical therapy if these signs and symptoms occur [see Warnings and Precautions (5.5), Use in Specific Populations (8.6)].

17.5Adverse Skin Reactions

Patients should be informed that CELEBREX is a sulfonamide and can cause serious skin side effects such as exfoliative dermatitis, SJS, and TEN, which may result in hospitalizations and even death. Although serious skin reactions may occur without warning, patients should be informed of the signs and symptoms of skin rash and blisters, fever, or other signs of hypersensitivity such as itching, and seek immediate medical advice when observing any indicative signs or symptoms.

Patients should be advised to stop CELEBREX immediately if they develop any type of rash and contact their physician as soon as possible.

Patients with prior history of sulfa allergy should not take CELEBREX [see Warnings and Precautions (5.8)].

17.6Weight Gain and Edema

Long-term administration of NSAIDs including CELEBREX has resulted in renal injury. Patients at greatest risk are those taking diuretics, ACE-inhibitors, angiotensin II antagonists, or with renal or liver dysfunction, heart failure, and the elderly [see Warnings and Precautions (5.3, 5.6), Use in Specific Populations (8)].

Patients should be instructed to promptly report to their physicians signs or symptoms of unexplained weight gain or edema following treatment with CELEBREX [see Warnings and Precautions (5.3)].

17.7Anaphylactoid Reactions

Patients should be informed of the signs and symptoms of an anaphylactoid reaction (e.g., difficulty breathing, swelling of the face or throat). Patients should be instructed to seek immediate emergency assistance if they develop any of these signs and symptoms [see Warnings and Precautions (5.7)].

17.8Effects During Pregnancy

Patients should be informed that in late pregnancy CELEBREX should be avoided because it may cause premature closure of the ductus arteriosus [see Warnings and Precautions (5.9), Use in Specific Populations (8.1)].

17.9Preexisting Asthma

Patients should be instructed to tell their physicians if they have a history of asthma or aspirin-sensitive asthma because the use of NSAIDs in patients with aspirin-sensitive asthma has been associated with severe bronchospasm, which can be fatal. Patients with this form of aspirin sensitivity should be instructed not to take Celebrex. Patients with preexisting asthma should be instructed to seek immediate medical attention if their asthma worsens after taking Celebrex [see Warnings and Precautions (5.13)].

LAB-0036-16.0

MEDICATION GUIDE

Medication Guide for Non-Steroidal Anti-Inflammatory Drugs (NSAIDs)

(See the end of this Medication Guide for a list of prescription NSAID medicines.)

What is the most important information I should know about medicines called Non-Steroidal Anti-Inflammatory Drugs (NSAIDs)?

NSAID medicines may increase the chance of a heart attack or stroke that can lead to death.

This chance increases:

- with longer use of NSAID medicines
  - in people who have heart disease

NSAID medicines should never be used right before or after a heart surgery called a "coronary artery bypass graft (CABG)."

NSAID medicines can cause ulcers and bleeding in the stomach and intestines at any time during treatment. Ulcers and bleeding:

- can happen without warning symptoms
- may cause death

The chance of a person getting an ulcer or bleeding increases with:

- taking medicines called "corticosteroids" and "anticoagulants"
- longer use
- smoking
- drinking alcohol
- older age
- having poor health

NSAID medicines should only be used:

- exactly as prescribed
- at the lowest dose possible for your treatment
- for the shortest time needed

What are Non-Steroidal Anti-Inflammatory Drugs (NSAIDs)?

NSAID medicines are used to treat pain and redness, swelling, and heat (inflammation) from medical conditions such as:

- different types of arthritis
- menstrual cramps and other types of short-term pain

Who should not take a Non-Steroidal Anti-Inflammatory Drug (NSAID)?

Do not take an NSAID medicine:

- if you had an asthma attack, hives, or other allergic reaction with aspirin or any other NSAID medicine
- for pain right before or after heart bypass surgery

Tell your healthcare provider:

- about all of your medical conditions.
- about all of the medicines you take. NSAIDs and some other medicines can interact with each other and cause serious side effects. Keep a list of your medicines to show to your healthcare provider and pharmacist.
- if you are pregnant. NSAID medicines should not be used by pregnant women late in their pregnancy.
- if you are breastfeeding. Talk to your doctor.

What are the possible side effects of Non-Steroidal Anti-Inflammatory Drugs (NSAIDs)?

Serious side effects include: | Other side effects include:
- heart attack - stroke - high blood pressure - heart failure from body swelling (fluid retention) - kidney problems including kidney failure - bleeding and ulcers in the stomach and intestine - low red blood cells (anemia) - life-threatening skin reactions - life-threatening allergic reactions - liver problems including liver failure - asthma attacks in people who have asthma | - stomach pain - constipation - diarrhea - gas - heartburn - nausea - vomiting - dizziness

Get emergency help right away if you have any of the following symptoms:

- shortness of breath or trouble breathing
- chest pain
- weakness in one part or side of your body

- slurred speech
- swelling of the face or throat

Stop your NSAID medicine and call your healthcare provider right away if you have any of the following symptoms:

- nausea
- more tired or weaker than usual
- itching
- your skin or eyes look yellow
- stomach pain
- flu-like symptoms

- vomit blood
- there is blood in your bowel movement or it is black and sticky like tar
- skin rash or blisters with fever
- unusual weight gain
- swelling of the arms and legs, hands and feet

These are not all the side effects with NSAID medicines. Talk to your healthcare provider or pharmacist for more information about NSAID medicines.

Call your doctor for medical advice about side effects. You may report side effects to FDA at 1-800-FDA-1088.

Other information about Non-Steroidal Anti-Inflammatory Drugs (NSAIDs)

- Aspirin is an NSAID medicine but it does not increase the chance of a heart attack. Aspirin can cause bleeding in the brain, stomach, and intestines. Aspirin can also cause ulcers in the stomach and intestines.
- Some of these NSAID medicines are sold in lower doses without a prescription (over –the –counter). Talk to your healthcare provider before using over –the –counter NSAIDs for more than 10 days.

NSAID medicines that need a prescription
Generic Name | Tradename
Celecoxib | Celebrex
Diclofenac | Cataflam, Voltaren, Arthrotec (combined with misoprostol)
Diflunisal | Dolobid
Etodolac | Lodine, Lodine XL
Fenoprofen | Nalfon, Nalfon 200
Flurbiprofen | Ansaid
Ibuprofen | Motrin, Tab-Profen, Vicoprofen [Vicoprofen contains the same dose of ibuprofen as over-the-counter (OTC) NSAIDs, and is usually used for less than 10 days to treat pain. The OTC NSAID label warns that long term continuous use may increase the risk of heart attack or stroke.] (combined with hydrocodone), Combunox (combined with oxycodone)
Indomethacin | Indocin, Indocin SR, Indo-Lemmon, Indomethagan
Ketoprofen | Oruvail
Ketorolac | Toradol
Mefenamic Acid | Ponstel
Meloxicam | Mobic
Nabumetone | Relafen
Naproxen | Naprosyn, Anaprox, Anaprox DS, EC-Naproxyn, Naprelan, Naprapac (copackaged with lansoprazole)
Oxaprozin | Daypro
Piroxicam | Feldene
Sulindac | Clinoril
Tolmetin | Tolectin, Tolectin DS, Tolectin 600

This Medication Guide has been approved by the U.S. Food and Drug Administration.

LAB-0609-1.0

PACKAGE LABEL

PRINCIPAL DISPLAY PANEL -